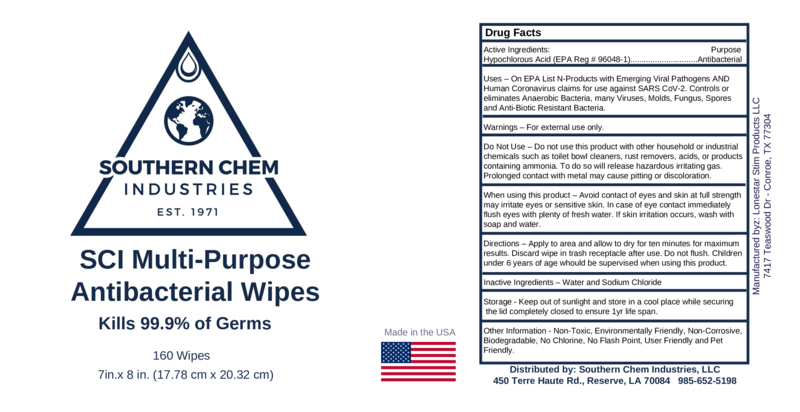 DRUG LABEL: SCI Multi-Purpose Antibacterial Wipes
NDC: 55549-100 | Form: CLOTH
Manufacturer: Southern Chem Industries LLC
Category: otc | Type: HUMAN OTC DRUG LABEL
Date: 20200915

ACTIVE INGREDIENTS: HYPOCHLOROUS ACID 5 g/100 g
INACTIVE INGREDIENTS: SODIUM CHLORIDE 16.26 g/100 g; WATER

SCI Antibacterial Wipes

1. Hypochlorous Acid
2. Sodium Chloride
3. Water.

Active Ingredient(s)

Hypochlorous Acid (EPA Reg # 96048-1) Antibacterial

Purpose

Antibacterial

Use

On EPA List N-Products with Emerging Viral Pathogens AND Human Coronavirus claims for use against SARS CoV-2. Controls or eliminates Anaerobic Bacteria, many Viruses, Molds, Fungus, Spores
and Anti-Biotic Resistant Bacteria.

Warnings

For external use only.

Do not use this product with other household or industrial chemicals such as toilet bowl cleaners, rust removers, acids, or products containing ammonia. To do so will release hazardous irritating gas. Prolonged contact with metal may cause pitting or discoloration.

WHEN USING

Avoid contact of eyes and skin at full strength may irritate eyes or sensitive skin. In case of eye contact immediately flush eyes with plenty of fresh water. If skin irritation occurs, wash with soap and water.

Stop use and ask a doctor if irritation or rash occurs. These may be signs of a serious condition.

Keep out of reach of children. If swallowed, get medical help or contact a Poison Control Center right away.

Directions

Apply to area and allow to dry for ten minutes for maximum results. Discard wipe in trash receptacle after use. Do not flush. Children under 6 years of age whould be supervised when using this product.

Other information

Storage - Keep out of sunlight and store in a cool place while securing
the lid completely closed to ensure 1yr life span.

Other Information - Non-Toxic, Environmentally Friendly, Non-Corrosive, Biodegradable, No Chlorine, No Flash Point, User Friendly and Pet Friendly.

Inactive ingredients

Water and Sodium Chloride